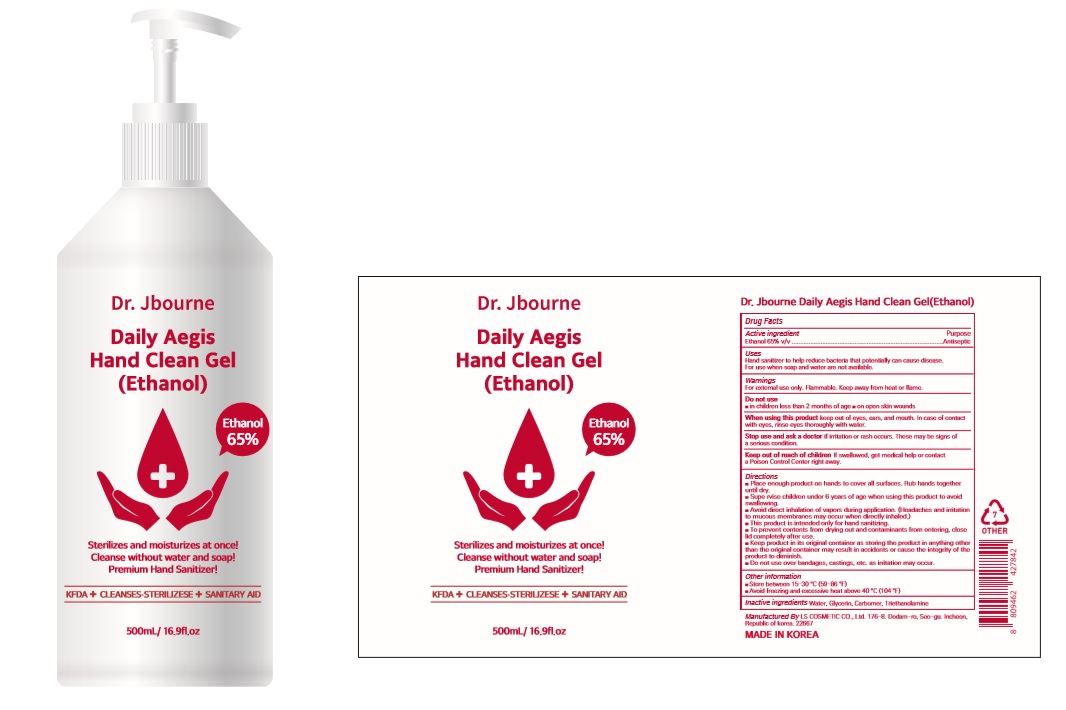 DRUG LABEL: Dr. Jbourne Daily Aegis Hand Clean Gel(Ethanol)
NDC: 59545-0565 | Form: GEL
Manufacturer: LS COSMETIC CO.,LTD.
Category: otc | Type: HUMAN OTC DRUG LABEL
Date: 20200413

ACTIVE INGREDIENTS: ALCOHOL 325 mL/500 mL
INACTIVE INGREDIENTS: GLYCERIN; CARBOMER HOMOPOLYMER, UNSPECIFIED TYPE; WATER; TROLAMINE

Dr. Jbourne Daily Aegis Hand Clean Gel(Ethanol) 500 ml : 59545-0565